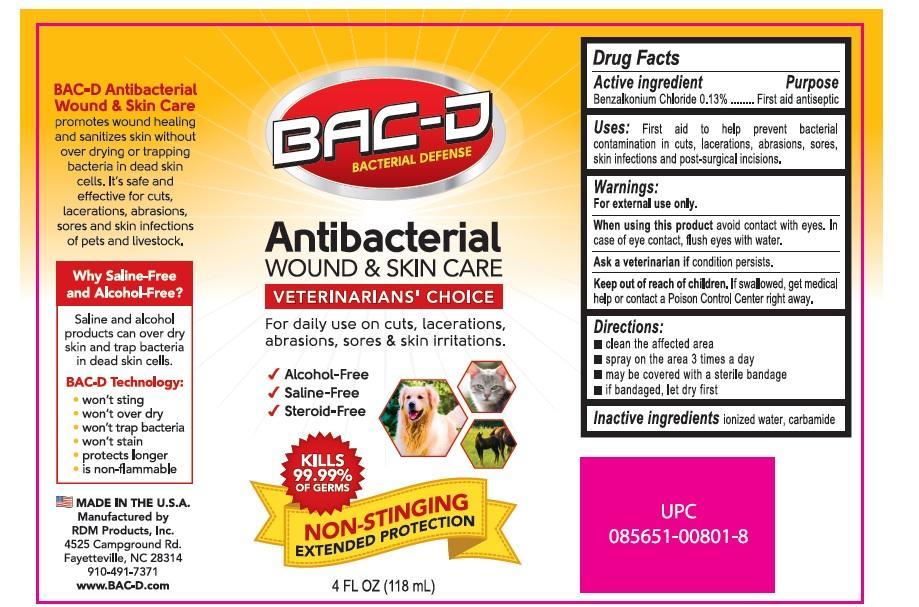 DRUG LABEL: BAC-D Antibacterial Wound and Skin care
NDC: 69082-500 | Form: SPRAY
Manufacturer: RDM Products, Inc
Category: otc | Type: HUMAN OTC DRUG LABEL
Date: 20151110

ACTIVE INGREDIENTS: BENZALKONIUM CHLORIDE 0.13 g/100 mL
INACTIVE INGREDIENTS: WATER; UREA

BAC-D Antibacterial Wound and Skin care

Active ingredient

Benzalkonium chloride 0.13 %

Purpose

First aid Product

Keep out of reach of children.

If swallowed, get medical help or contact a Poison Control Center right away.

Uses

First aid to help prevent the risk of bacterial contamination in minor cuts, scrapes, burns and post-surgical incision sites.

Warnings

For external use only.

Do not use

- in the eyes or apply over large areas of the body longer than 1 week unless directed by a doctor

Directions for use

- Clean the affected area
- Spray a small amount of this product on the area 1 to 3 times a day.
- May be covered with a sterile bandage
- If bandaged let dry first

Inactive ingredients

Ionized water, Carbamide

Made in the U.S.A

Manufactured for

RDM Products Inc.

910-491-7371

PO Box 35003

Fayetteville, NC 28303

www.BAC-D.com